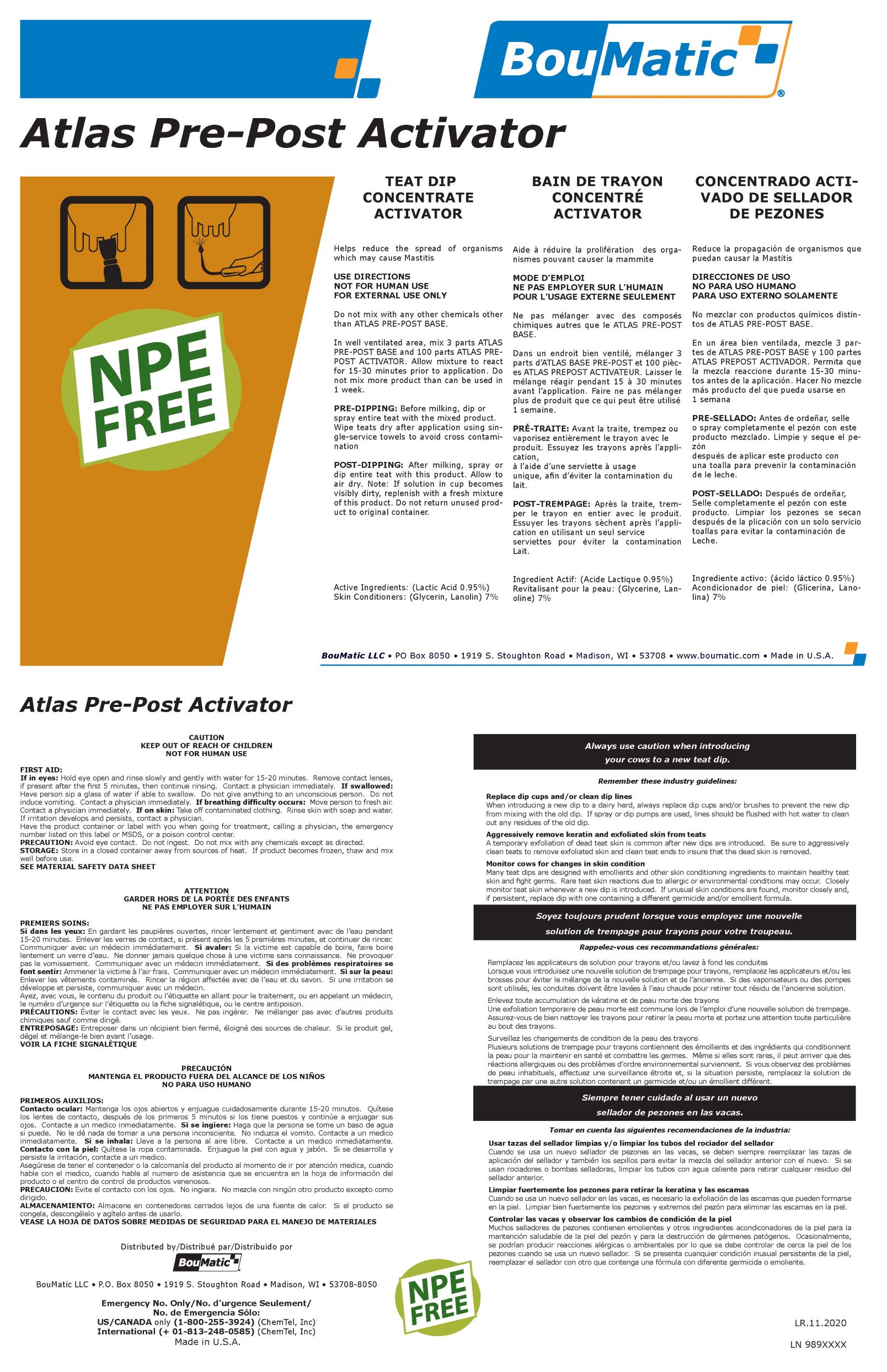 DRUG LABEL: Atlas PrePost Activator
NDC: 48106-2034 | Form: LIQUID
Manufacturer: BOUMATIC, LLC
Category: animal | Type: OTC ANIMAL DRUG LABEL
Date: 20210316

ACTIVE INGREDIENTS: LACTIC ACID 9500 [ppm]/1 g
INACTIVE INGREDIENTS: GLYCERIN 55000 [ppm]/1 g; PEG-75 LANOLIN 10000 [ppm]/1 g; WATER 909500 [ppm]/1 g; SODIUM HYDROXIDE 1000 [ppm]/1 g

Atlas PrePost Activator

Claim of effectiveness.

Helps reduce the spread of organisms
which may cause Mastitis

Use Directions

In well ventilated area, mix 3 parts ATLAS
PRE-POST BASE and 100 parts ATLAS PREPOST
ACTIVATOR. Allow mixture to react
for 15-30 minutes prior to application. Do
not mix more product than can be used in
1 week.
PRE-DIPPING: Before milking, dip or
spray entire teat with the mixed product.
Wipe teats dry after application using single-
service towels to avoid cross contamination
POST-DIPPING: After milking, spray or
dip entire teat with this product. Allow to
air dry. Note: If solution in cup becomes
visibly dirty, replenish with a fresh mixture
of this product. Do not return unused product
to original container.

First Aid

If in eyes: Hold eye open and rinse slowly and gently with water for 15-20 minutes. Remove contact lenses,
if present after the first 5 minutes, then continue rinsing. Contact a physician immediately. If swallowed:
Have person sip a glass of water if able to swallow. Do not give anything to an unconscious person. Do not
induce vomiting. Contact a physician immediately. If breathing difficulty occurs: Move person to fresh air.
Contact a physician immediately. If on skin: Take off contaminated clothing. Rinse skin with soap and water.
If irritation develops and persists, contact a physician.
Have the product container or label with you when going for treatment, calling a physician, the emergency
number listed on this label or MSDS, or a poison control center.

Precautions & Hazards

PRECAUTION: Avoid eye contact. Do not ingest. Do not mix with any chemicals except as directed.

General Storage

STORAGE: Store in a closed container away from sources of heat. If product becomes frozen, thaw and mix
well before use.

Claim of effectiveness.

Helps reduce the spread of organisms
which may cause Mastitis